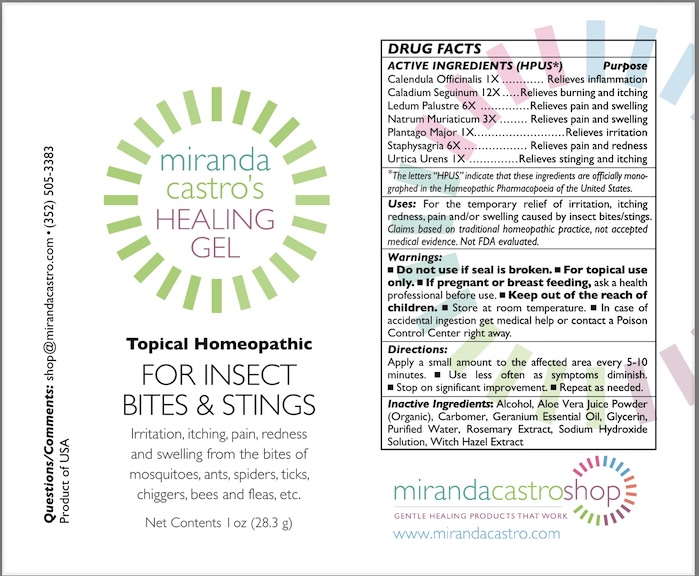 DRUG LABEL: miranda castros HEALING FOR INSECT BITES  AND STINGS
NDC: 82586-500 | Form: GEL
Manufacturer: MIRANDA CASTRO'S SHOP, LLC
Category: homeopathic | Type: HUMAN OTC DRUG LABEL
Date: 20251023

ACTIVE INGREDIENTS: LEDUM PALUSTRE WHOLE 6 [hp_X]/1 g; DELPHINIUM STAPHISAGRIA SEED 6 [hp_X]/1 g; CALENDULA OFFICINALIS FLOWER 1 [hp_X]/1 g; SODIUM CHLORIDE 3 [hp_X]/1 g; URTICA URENS 1 [hp_X]/1 g; DIEFFENBACHIA SEGUINE 12 [hp_X]/1 g; PLANTAGO MAJOR 1 [hp_X]/1 g
INACTIVE INGREDIENTS: GERANIUM OIL, ALGERIAN TYPE; SODIUM HYDROXIDE; ROSEMARY OIL; WITCH HAZEL; GLYCERIN; CARBOMER HOMOPOLYMER, UNSPECIFIED TYPE; ALCOHOL; WATER; ALOE VERA LEAF; CARBOMER HOMOPOLYMER TYPE C

miranda castro's HEALING GEL FOR INSECT BITES & STINGS

Active ingredientes*

Calendula Officinalis 1X

Caladium Seguinum 12X

Ledum Palustre 6X

Natrum Muriaticum 3X

Plantago Major 1X

Staphysagria 6X

Urtica Urens 1X

The letters "HPUS" indicate that the component in this product is officially monographed in the Homeopathic Pharmacopoeia of the United States.

Purpose*

Calendula Officinalis...Relieves inflammation

CaladiumSeguinumI...Relieves burning and itching

Ledum Palustre6X .... Relieves pain and swelling

Natrum Muriaticum.....Relieves pain and swelling

PlantagoMajor............Relieves irritation

Staphysagria..............Relievespain and redness

Urtica Urens...............Relieves stinging and itching

Uses*

For the temporary relief of irritation, itching redness, pain and/or swelling caused by insect bites/stings.

*Claims based on traditional homeopathic practice, not accepted medical evidence. Not FDA evaluated.

Warnings

• Do not use if seal is broken. • For topical use only. • Store at room temperature.

• Keep out of the reach of children. • In case of accidental ingestion get medical help or contact a Poison Control Center right away.

Pregnant or breast-feeding

If pregnant or breast feeding, ask a health professional before use.

Directions

Apply a small amount to the affected area every 5-10 minutes. Use less often as symptoms diminish.

• Stop on significant improvement. • Repeat as needed.

Inactive Ingredients

Inactive Ingredients: Alcohol, Aloe Vera Juice Powder (Organic), Carbomer, Geranium Essential Oil, Glycerin, Purified Water, Rosemary Extract, Sodium Hydroxide Solution, Witch Hazel Extract